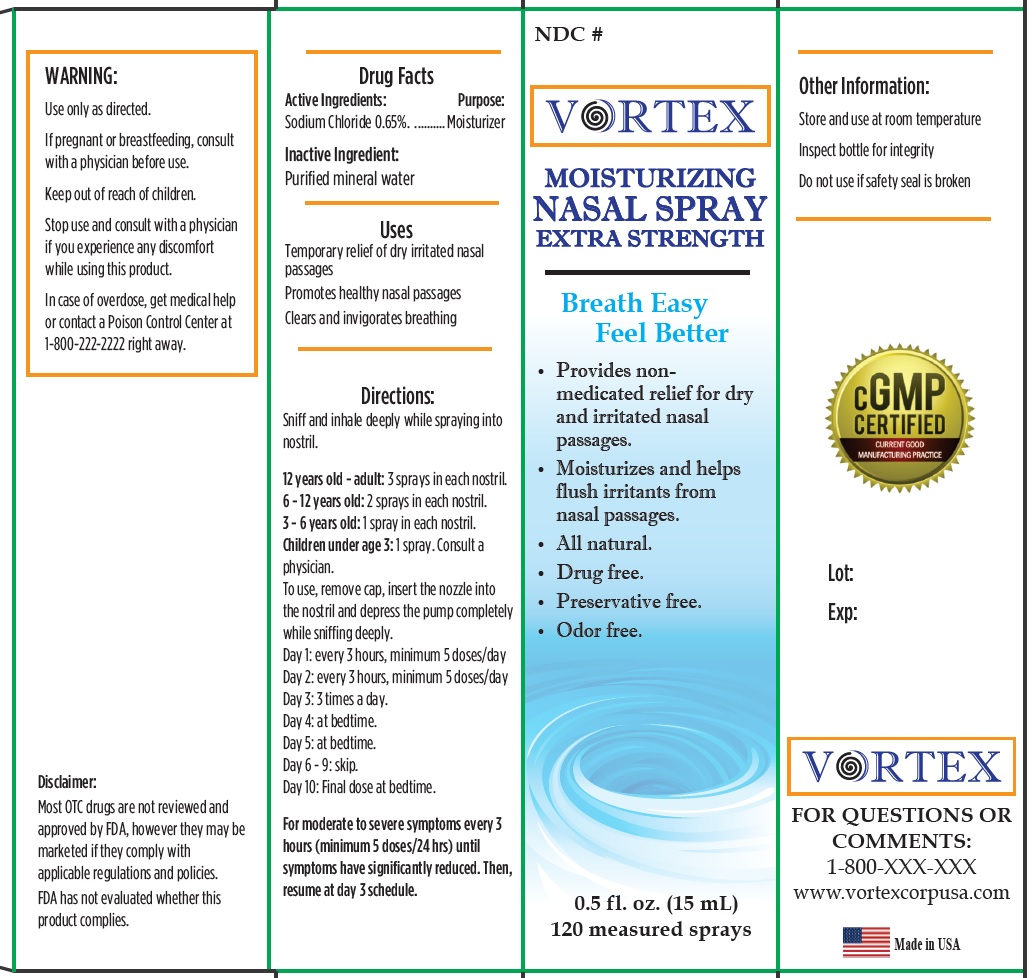 DRUG LABEL: Vortex Moisturizer Nasal
NDC: 82529-000 | Form: LIQUID
Manufacturer: Vortex Life Sciences, Inc.
Category: otc | Type: HUMAN OTC DRUG LABEL
Date: 20220307

ACTIVE INGREDIENTS: SODIUM CHLORIDE 6.5 mg/1 mL
INACTIVE INGREDIENTS: WATER

Vortex Moisturizer Nasal Spray

Active Ingredients:

Sodium Chloride 0.65%

Purpose:

Moisturizer

Inactive Ingredient:

Purified mineral water

Uses

Temporary relief of dry irritated nasal passages
Promotes healthy nasal passages
Clears and invigorates breathing

Directions:

Sniff and inhale deeply while spraying into nostril.
12 years old- adult: 3 sprays in each nostril.
6 - 12 years old: 2 sprays in each nostril.
3 - 6 years old: 1 spray in each nostril.
Children under age 3: 1 spray. Consult a
physician.
To use, remove cap, insert the nozzle into
the nostril and depress the pump completely
while sniffing deeply.
Day 1: every 3 hours, minimum 5 doses/day
Day 2: every 3 hours, minimum 5 doses/day
Day 3: 3 times a day.
Day 4: at bedtime.
Day 5: at bedtime.
Day 6 - 9: skip.
Day 10: Final dose at bedtime.
For moderate to severe symptoms every 3 hours (minimum 5 doses/24 hrs) until symptoms have significantly reduced. Then,
resume at day 3 schedule.

WARNING:

Use only as directed.

If pregnant or breastfeeding,

consult with a physician before use.

Stop use and consult with a physician

if you experience any discomfort while using this product.

In case of overdose, get medical help or contact a Poison Control Center at 1-800-222-2222 right away.

Other Information:

Store and use at room temperature Inspect bottle for integrity Do not use if safety seal is broken